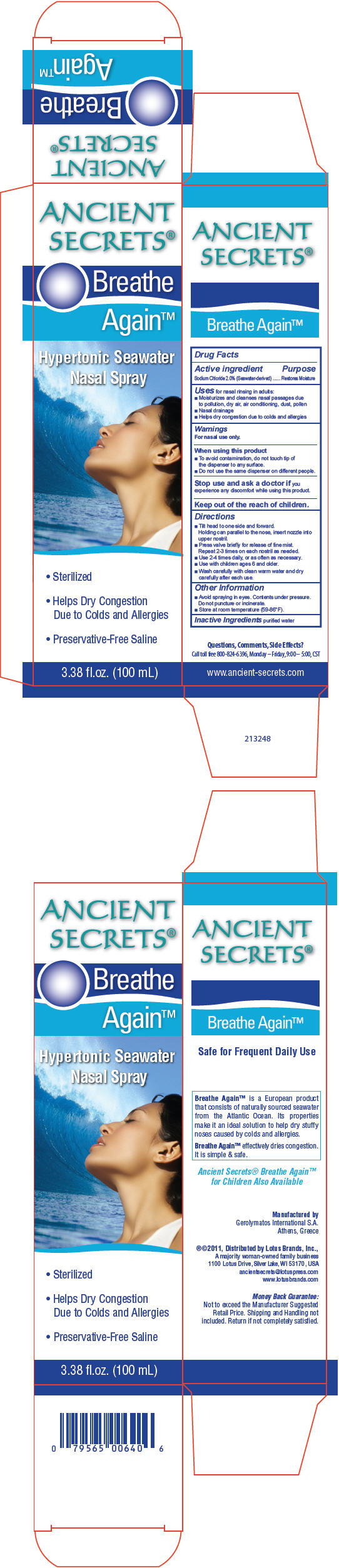 DRUG LABEL: Ancient Secrets 
NDC: 76328-100 | Form: AEROSOL, SPRAY
Manufacturer: LOTUS BRANDS, INC.
Category: otc | Type: HUMAN OTC DRUG LABEL
Date: 20241218

ACTIVE INGREDIENTS: Sodium Chloride 20 mg/100 mL
INACTIVE INGREDIENTS: Water

ANCIENT
SECRETS®
Breathe
Again™
Hypertonic Seawater
Nasal Spray

Drug Facts

Active ingredient

Sodium Chloride 2.0% (Seawater-derived)

Purpose

Restores Moisture

Uses

for nasal rinsing in adults:

- Moisturizes and cleanses nasal passages due to pollution, dry air, air conditioning, dust, pollen
- Nasal drainage
- Helps dry congestion due to colds and allergies

Warnings

For nasal use only.

When using this product

- To avoid contamination, do not touch tip of the dispenser to any surface.
- Do not use the same dispenser on different people.

Stop use and ask a doctor if you experience any discomfort while using this product.

Keep out of the reach of children.

Directions

- Tilt head to one side and forward.
  Holding can parallel to the nose, insert nozzle into upper nostril.
- Press valve briefly for release of fine mist.
  Repeat 2-3 times on each nostril as needed.
- Use 2-4 times daily, or as often as necessary.
- Use with children ages 6 and older.
- Wash carefully with clean warm water and dry carefully after each use.

Other Information

- Avoid spraying in eyes. Contents under pressure. Do not puncture or incinerate.
- Store at room temperature (59-86°F).

Inactive Ingredients

purified water

Questions, Comments, Side Effects?

Call toll free 800-824-6396, Monday – Friday, 9:00 – 5:00, CST

Manufactured by
Gerolymatos International S.A.
Athens, Greece

®©2011, Distributed by Lotus Brands, Inc.,
A majority woman-owned family business
1100 Lotus Drive, Silver Lake, WI 53170, USA

PRINCIPAL DISPLAY PANEL - 100 mL Bottle Carton

ANCIENT
SECRETS®

Breathe
Again™

Hypertonic Seawater
Nasal Spray

- Sterilized
- Helps Dry Congestion
  Due to Colds and Allergies
- Preservative-Free Saline

3.38 fl.oz. (100 mL)